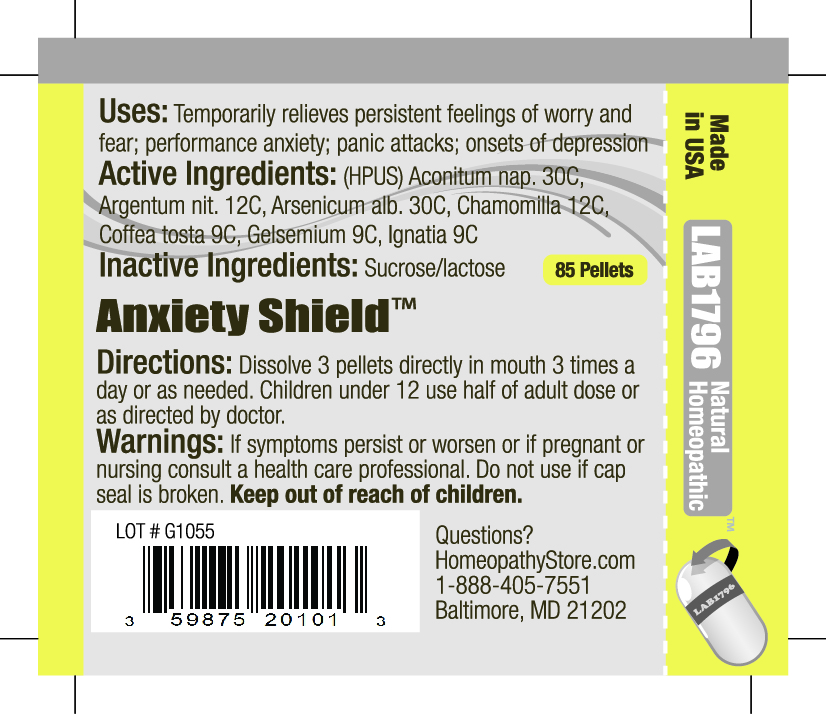 DRUG LABEL: Lab1796 Anxiety Shield
NDC: 59875-2010 | Form: PELLET
Manufacturer: HomeopathyStore.com
Category: homeopathic | Type: HUMAN OTC DRUG LABEL
Date: 20101230

ACTIVE INGREDIENTS: ACONITUM NAPELLUS 30 [hp_C]/1 1; SILVER NITRATE 12 [hp_C]/1 1; ARSENIC TRIOXIDE 30 [hp_C]/1 1; MATRICARIA RECUTITA 12 [hp_C]/1 1; COFFEE BEAN 9 [hp_C]/1 1; GELSEMIUM SEMPERVIRENS ROOT 9 [hp_C]/1 1; STRYCHNOS IGNATII SEED 9 [hp_C]/1 1
INACTIVE INGREDIENTS: SUCROSE; LACTOSE

Anxiety Shield

Uses:

Temporarily relieves persistent feelings of worry and fear; performance anxiety; panic attacks; onsets of depression

Active Ingredients:

(HPUS) Aconitum nap. 30C, Argentum nit. 12C, Arsenicum alb. 30C, Chamomilla 12C, Coffea tosta 9C, Gelsemium 9C, Ignatia 9C

Inactive Ingredients:

Sucrose/lactose

Directions:

DOSAGE AND ADMINISTRATION

Dissolve 3 pellets directly in mouth 3 times a day or as needed. Children under 12 use half of adult dose or as directed by doctor.

Warnings:

If symptoms persist or worsen or if pregnant or nursing consult a health care professional. Do not use if cap seal is broken.

Keep out of reach of children.